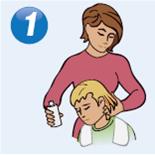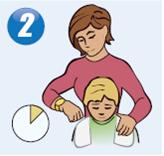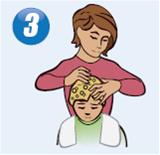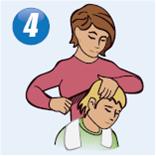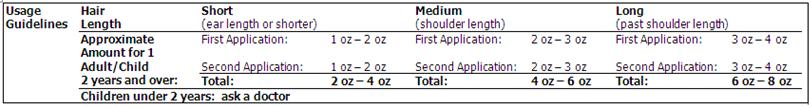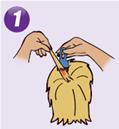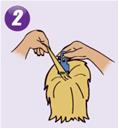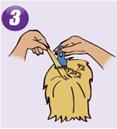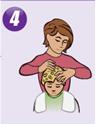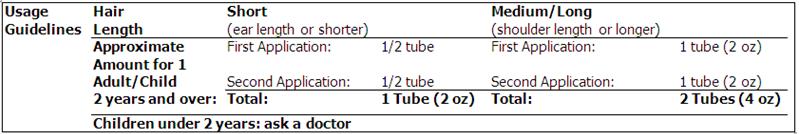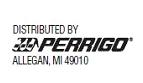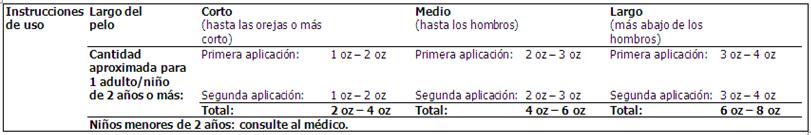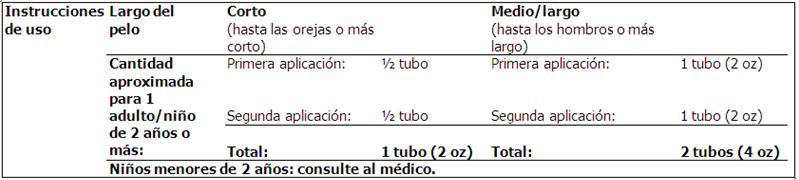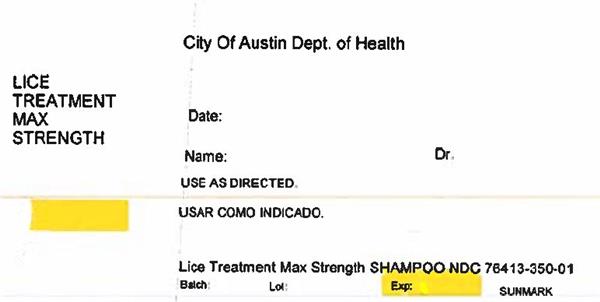 DRUG LABEL: Sunmark Lice Killing
NDC: 76413-350 | Form: SHAMPOO
Manufacturer: Central Texas Community Health Centers
Category: otc | Type: HUMAN OTC DRUG LABEL
Date: 20180607

ACTIVE INGREDIENTS: PIPERONYL BUTOXIDE 4 g/100 mL; PYRETHRUM EXTRACT 0.33 g/100 mL
INACTIVE INGREDIENTS: BENZYL ALCOHOL; WATER; C13-14 ISOPARAFFIN; XANTHAN GUM

McKesson Lice Killing Shampoo Drug Facts

Active ingredients

Piperonyl butoxide 4%

Pyrethrum extract (equivalent to 0.33% pyrethrins)

Purpose

Lice treatment

Uses

treats head, pubic (crab), and body lice

Warnings

For external use only

Do not use

- near eyes
- inside nose, mouth, or vagina
- on lice in eyebrows or eyelashes. See a doctor if lice are present in these areas.

Ask a doctor before use if you are

allergic to ragweed. May cause breathing difficulty or an asthmatic attack.

When using this product

- keep eyes tightly closed and protect eyes with a washcloth or towel
- if product gets into eyes, flush with water right away
- scalp itching or redness may occur

Stop use and ask a doctor if

- breathing difficulty occurs
- eye irritation occurs
- skin or scalp irritation continues or infection occurs

Keep out of reach of children.

If swallowed, get medical help or contact a Poison Control Center right away.

Directions

Shake well before using

- Important: Read warnings before use

Adults and children 2 years and over:

Inspect

- check each household member with a magnifying glass in bright light for lice/nits (eggs)
- look for tiny nits near scalp, beginning at back of neck and behind ears
- examine small sections of hair at a time
- unlike dandruff which moves when touched, nits stick to the hair
- if either lice or nits are found, treat with this product

Treat

- apply thoroughly to DRY HAIR or other affected area. For head lice, first apply behind ears and to back of neck.
- allow product to remain for 10 minutes, but no longer
- use warm water to form a lather, shampoo, then thoroughly rinse
- for head lice, towel dry hair and comb out tangles

Remove lice and their eggs (nits)

- use a fine-tooth or special lice/nit comb. Remove any remaining nits by hand (using a throw-away glove).
- hair should remain slightly damp while removing nits
- if hair dries during combing, dampen slightly with water
- for head lice, part hair into sections. Do one section at a time starting on top of the head. Longer hair may take 1 to 2 hours.
- lift a 1-to 2-inch wide strand of hair. Place comb as close to scalp as possible and comb with a firm, even motion away from scalp.
- pin back each strand of hair after combing
- clean comb often. Wipe nits away with tissue and discard in a plastic bag. Seal bag and discard to prevent lice from coming back.
- after combing, thoroughly recheck for lice/nits. Repeat combing if necessary.
- check daily for any lice/nits that you missed
- a second treatment must be done in 7 to 10 days to kill any newly hatched lice
- if infestation continues, see a doctor for other treatments
- Children under 2 years: ask a doctor

Other information

- store at 20°-25°C (68°-77°F)
- keep carton for important product information
- see package insert for additional information

Inactive ingredients

benzyl alcohol, C13-C14 isoparaffin, fragrance, polyoxyethylene (1,1,3,3-tetramethyl butyl) phenyl ether, water, xanthan gum

Questions or comments?

1-800-719-9260

Consumer Information

Steps to Success

with 1-2-3 Lice Control System

Complete lice control for your family and home

Step 1: Treat

Lice Killing Shampoo

See Usage Guidelines below to estimate how much product you will need.

Inspect

• check each household member with a magnifying glass in bright light for lice/nits (eggs)

• look for tiny nits near scalp, beginning at back of neck and behind ears

• examine small sections of hair at a time

• unlike dandruff which moves when touched, nits stick to the hair

• if either lice or nits are found, treat with this product

NOTE:

• Use towels to protect child's eyes from treatment and prevent clothes from getting wet.

• Apply Lice Killing Shampoo thoroughly to DRY HAIR or other affected area.

• Wetting the hair dilutes the treatment making it less effective.

• Also, lice can hold their breath when immersed in water making it difficult for the active ingredient to penetrate the lice.

• For head lice, thoroughly massage shampoo into scalp, behind the ears and to the back of the neck. Lice can crawl up and down the shaft of the hair very quickly so it is important to apply the treatment from the roots to the ends of the hair.

• Allow product to remain on the hair (or other affected area) for 10 minutes, but no longer.

• Add warm water and massage to form a lather.

• Rinse thoroughly.

• For head lice, towel dry hair and comb out tangles.

• Proceed to Step 2.

• A second treatment must be done in 7 to 10 days to kill any newly hatched lice.

Step 2: Remove

Egg & Nit Combing Gel

This product should be used AFTER Lice Killing Shampoo (Step 1). Combing out eggs & nits* is an essential step to complete lice control.

See Usage Guidelines below to estimate how much product you will need.

NOTE:

• A fine-toothed comb or a special lice/nit removing comb (included) must be used to remove lice, eggs, and nits from hair.

• Before starting have on hand:

- extra towels

- bobby pins or hair clips

- facial tissues or paper towels

- regular comb for parting and detangling hair

- throw-away gloves

• Find a distraction for your child (e.g. books, TV, game).

• Comb out damp hair with a regular wide-tooth comb to take out snarls and tangles.

• Apply Egg & Nit Combing Gel to one section of hair. (Do not apply to entire head at once, since gel dries quickly.)

• Massage thoroughly until all strands of hair in this section are covered with the gel.

• When combing, use the fine-toothed lice/nit comb provided and make sure the teeth are facing you.

• Part hair into sections. Do one section at a time starting on top of head. Longer hair may take 1 to 2 hours.

• Lift a small strand of hair (about 1-2" thick) from the section with the gel.

• Begin combing in a "scooping" motion: gently push the teeth as close to the scalp as possible and drag comb firmly and evenly from the scalp to the ends of the hair (newly-laid eggs are found near the roots of the hair so it is important to get the teeth very close to the scalp). Make sure the teeth are deeply embedded into the strands as you comb through.

• Always comb away from the head.

• Wipe eggs and nits from the teeth of the comb often with a tissue or paper towel.

• Remove any remaining nits by hand (using a throw-away glove).

• Discard all the used tissues or cloths into a sealed plastic bag and dispose of immediately to prevent lice from coming back.

• Pin back the strand you just finished combing with a bobby pin or hair clip.

• Lift up another 1-2 inch strand with gel and repeat the combing procedure.

• When one section with gel has been combed and pinned, apply Egg & Nit Combing Gel to another section of hair. Continue to comb hair 1-2 inches at a time until entire head has been combed and pinned.

• Keep the hair damp during combing. If hair dries during combing, dampen slightly with water, and re-apply Egg & Nit Combing Gel as needed.

• After you have combed and pinned the entire head, remove all bobby pins or hair clips and thoroughly recheck for lice/nits. Repeat combing if necessary. Rinse hair thoroughly with warm water. If desired, you may also wash with regular shampoo.

* Nits are empty eggshells left behind when lice hatch from eggs.

Step 3: Control

Lice Control Spray

Use Lice Control Spray to kill lice and their eggs on mattresses, furniture, car interiors and other non-washable items.

• Use Lice Control Spray to kill lice and their eggs on mattresses, furniture, car interiors and other non-washable items. A regular disinfectant spray will not kill lice and their eggs.

• After spraying the infested area, vacuum rugs and carpets. Dispose of the vacuum cleaner bags after use.

• Wash all clothes, towels, washable hats, scarves, coats and bed linens in hot water. Dry in high heat for at least 20 minutes.

• Dry clean non-washables.

• Personal combs and brushes may be disinfected by soaking in hot water (above 130°F) for at least 10 minutes.

• Place stuffed toys in plastic bags and seal them for 4 weeks.

• Disinfectant Checklist

- Home and auto upholstery

- Mattresses, pillows, pillowcases

- Bed linen

- Towels

- Stuffed animals, toys

- Headphones

- Hats

- Headbands

- Bike/sports helmets

- Coats, scarves, earmuffs, gloves

- Play mats

- Clothing

- Barrettes/hair ornaments

- Hair rollers

- Combs and brushes

- Baseball caps

Daily Checking

TO PREVENT REINFESTATION:

• Carefully inspect infested family member daily for at least 2 weeks. If you see eggs or nits, repeat Step 2.

• Check other family members for Head Lice. If anyone in the family is infested, follow Step 1 and Step 2. Repeat Step 3 with any articles or items with which they have come into contact.

Second Application

Repeat the same procedures within 7-10 days for

Step 1: Treat and Step 2: Remove

There may be some eggs that were not combed out after the first treatment. These eggs will hatch and need to be killed with the second treatment.

If infestation continues, see a doctor for other treatments.

Did You Know?

Head Lice

• lay small white eggs (nits) on hair shaft close to scalp

• nits are most easily found on back of neck or behind ears

• disinfect hats, hair ribbons, scarves, coats, towels, and bed linens by machine washing in hot water (above 54°C (130°F)), then using hottest dryer cycle for at least 20 minutes

• items that cannot be washed (bedspreads, blankets, pillows, stuffed toys, etc.) should be dry-cleaned or sealed in a plastic bag for 4 weeks, then removed outdoors and shaken out very hard before using again

• items that cannot be washed, dry-cleaned, or stored may be sprayed with a product designed for this purpose

• soak all combs and brushes in hot water (above 54°C (130°F)) for at least 10 minutes

• vacuum all carpets, mattresses, upholstered furniture, and car seats that may have been used by affected people

Pubic (Crab) Lice

• may be transmitted by sexual contact. Sexual partners should be treated simultaneously to avoid reinfestation

• lice are very small and look like brown or grey dots on skin

• usually cause intense itching and lay small white eggs (nits) on the hair shaft generally close to the skin surface

• may be present on the short hairs of groin, thighs, trunk, and underarms, and occasionally on the beard and mustache

• disinfect underwear by machine washing in hot water (above 54°C (130°F)), then using hottest dryer cycle for at least 20 minutes

Body Lice

• body lice and their eggs (nits) are generally found in the seams of clothing particularly in waistline and armpit area

• body lice feed on skin then return to clothing to lay their eggs

• disinfect clothing by machine washing in hot water (above 54°C (130°F)), then using hottest dryer cycle for at least 20 minutes

• do not seal clothing in a plastic bag because nits can remain dormant for up to 30 days

Save this insert for future reference

Keep carton for important product information.

Lice Killing Shampoo

Drug Facts

Active ingredients Purpose

Piperonyl butoxide 4%...............................................................................................Lice treatment

Pyrethrum extract

(equivalent to 0.33% pyrethrins)................................................................................Lice treatment

Uses treats head, pubic (crab), and body lice

Warnings

For external use only

Do not use

- near eyes • inside nose, mouth, or vagina
- on lice in eyebrows or eyelashes. See a doctor if lice are present in these areas.

Ask a doctor before use if you are • allergic to ragweed. May cause breathing difficulty or an asthmatic attack.

When using this product

- keep eyes tightly closed and protect eyes with a washcloth or towel
- if product gets in eyes, flush with water right away
- scalp itching or redness may occur

Stop use and ask a doctor if

- breathing difficulty occurs
- eye irritation occurs
- skin or scalp irritation continues or infection occurs

Keep out of reach of children. If swallowed, get medical help or contact a Poison Control Center right away. (1-800-222-1222)

Directions

Shake well before using

- Important: Read warnings before use

Other information

- store at 20°-25°C (68°-77°F)

Inactive ingredients benzyl alcohol, C13-C14 isoparaffin, fragrance, polyoxyethylene (1,1,3,3-tetramethyl butyl) phenyl ether, purified water, xanthan gum

Questions or comments? 1-800-719-9260

Egg & Nit Combing Gel

Product Facts

Use to make egg and nit removal from the hair faster and easier

Warnings

For external use only. Keep out of reach of children.

Ingredients: purified water, glycerin, hydroxyethylcellulose, PG-hydroxyethylcellulose cocodimonium chloride, polysorbate 20, DMDM hydantoin, fragrance, iodopropynyl butylcarbamate

Store at 20°-25°C (68°-77°F)

Lice Control Spray

Product Facts

ACTIVE INGREDIENT:

*Permethrin.........................................................................................................................0.50%

**OTHER INGREDIENTS:....................................................................................99.50%

100.00%

*Cis/trans ratio: Min. 35% (+/-) cis and Max. 65% (+/-) trans.

**Contains Petroleum distillate

PRECAUTIONARY STATEMENTS

HAZARDS TO HUMANS

CAUTION: Harmful if swallowed or absorbed through skin. Avoid inhalation of spray mist. Causes eye irritation. Avoid contact with skin, eyes or clothing. Wash thoroughly with soap and water after handling. Avoid contamination of feed and foodstuffs.

PHYSICAL OR CHEMICAL HAZARDS

Contents under pressure. Do not use or store near heat or open flame. Do not puncture or incinerate container. Exposure to temperatures above 130°F (54°C) may cause bursting.

FIRST AID

Call a Poison Control Center or doctor immediately for treatment advice. Have product container or label with you when calling a Poison Control Center or doctor or going for treatment.

If swallowed:

- Immediately call a Poison Control Center or doctor.
- Do not induce vomiting unless told to do so by a Poison Control Center or doctor.
- Do not give any liquid to the person.
- Do not give anything by mouth to an unconscious person.

If in eyes:

- Hold eye open and rinse slowly and gently with water for 15-20 minutes.
- Remove contact lenses, if present, after the first 5 minutes, then continue rinsing eye.

If inhaled:

- Move person to fresh air.
- If person is not breathing, call 911 or an ambulance, then give artificial respiration, preferably by mouth-to-mouth, if possible.

If on skin or clothing:

- Take off contaminated clothing.
- Rinse skin immediately with plenty of water for 15-20 minutes.

NOTE TO PHYSICIAN

Contains petroleum distillate – vomiting may cause aspiration pneumonia.

DIRECTIONS FOR USE

It is a violation of Federal law to use this product in a manner inconsistent with its labeling. Remove pets and birds and cover fish aquaria before space spraying or surface applications.

This product is not for use on humans. If lice infestation occurs on humans, use a product labeled for use on humans. Vacate room after treatment and ventilate before reoccupying. Do not allow children or pets to contact treated areas until surfaces are dry.

SHAKE WELL BEFORE USING

Remove protective cap. Hold container upright and spray from a distance of 8-10 inches. Individuals with asthma or severe allergies should consult their doctor before using this product and have someone else apply this product.

To kill lice and louse eggs: Spray in an inconspicuous area to test for possible staining or discoloration. Inspect again after drying, then proceed to spray entire area to be treated. Hold container upright with nozzle away from you. Depress valve and spray from a distance of 8 to 10 inches. Spray each square foot for three seconds. Spray to the point of dampness but not run-off. Spray only those articles and parts of bedding including mattresses and furniture, that cannot be either laundered or dry-cleaned. Do not use on pillowcases, sheets or clothing. Allow all sprayed articles to dry thoroughly before each use.

STORAGE AND DISPOSAL

Storage: Store in a cool, dry area away from children and pets and away from heat, sparks and open flame. Do not transport or store below 32°F (0°C).

Container disposal: Do Not Puncture or Incinerate.

If empty: Place in trash or offer for recycling if available.

If partly filled: Call your local solid waste agency or 1-800-CLEANUP for disposal instructions. Never place unused product down any indoor or outdoor drain.

NOTICE: Purchaser assumes all responsibility for safety and use not in accordance with directions.

See carton for EPA numbers.

Pasos para el éxito

con el Sistema para el Control de la Pediculosis 1-2-3

Control completo de la pediculosis para su familia y el hogar

Paso 1: Tratar

Champú para la pediculosis

Véase las instrucciones de más abajo para calcular cuánto producto necesitará.

Inspeccione

• revise a cada miembro de la familia con una lupa en un lugar con buena luz en busca de piojos/liendres (huevos).

• busque pequeñas liendres cerca del cuero cabelludo, comenzando por la nuca y detrás de las orejas.

• examine pequeñas secciones de pelo a la vez.

• a diferencia de la caspa, que se mueve cuando uno la toca, las liendres están adheridas al pelo.

• si encuentra piojos o liendres, trátelos con este producto.

NOTA:

• Use toallas para proteger los ojos de los niños durante el tratamiento y para que no se humedezca la ropa.

• Aplique el champú para la pediculosis generosamente sobre el PELO SECO o en otras áreas afectadas.

• Si humedece el pelo, el tratamiento se diluye y eso lo hace menos efectivo.

• Además, los piojos pueden mantener la respiración cuando están sumergidos bajo el agua, lo que vuelve más difícil que el ingrediente activo penetre a los piojos.

• Para los piojos de la cabeza, masajee muy bien con el champú sobre el cuero cabelludo, detrás de las orejas y en la nuca. Los piojos pueden subir y bajar por el pelo muy rápido por lo que es importante aplicar el tratamiento desde las raíces hasta las puntas del pelo.

• Deje que el producto permanezca en el pelo (o en otras áreas afectadas) por 10 minutos, pero no más.

• Agregue agua tibia y masajee para hacer espuma.

• Enjuague con abundante agua.

• Para los piojos de la cabeza, seque el pelo con toalla y desenrede con un peine.

• Continúe con el Paso 2.

• Se debe realizar un segundo tratamiento dentro de 7 a 10 días para matar los piojos recién nacidos.

Paso 2: Remover

Gel Removedor de Huevos y Liendres

Este producto debe utilizarse LUEGO del Champú para la pediculosis (Paso 1). Remover los huevos y las liendres* es un paso esencial para completar el control de la pediculosis.

Véase las instrucciones de más abajo para calcular cuánto producto necesitará.

NOTA:

• Se debe usar un peine de dientes finos o un peine especial (incluido) para remover los piojos, los huevos y las liendres del pelo.

• Antes de empezar tenga a mano:

- toallas extra,

- horquillas o hebillas para el pelo,

- pañuelos o toallas de papel,

- peine común para separar y desenredar el pelo,

- guantes descartables.

• Busque una distracción para su hijo (por ejemplo, libros, televisión, juegos).

• Peine el pelo húmedo con un peine de dientes anchos para desenredarlo.

• Aplique el Gel Removedor de Huevos y Liendres a una parte del pelo. (No aplique en toda la cabeza de una sola vez, ya que el gel se seca rápido).

• Masajee muy bien hasta que todo el pelo en esta sección esté cubierto con el gel.

• Cuando peine, use el peine fino suministrado y asegúrese de que los dientes miren hacia usted.

• Separe el pelo en secciones. Haga una sección a la vez partiendo desde la coronilla. El cabello más largo puede demorar entre 1 y 2 horas.

• Levante un pequeño mechón de pelo (alrededor de 1-2” de ancho) de la sección con gel.

• Comience a peinar con un movimiento “de onda”: suavemente coloque los dientes lo más cerca posible del cuero cabelludo y arrastre el peine de manera firme y pareja desde el cuero cabelludo hasta las puntas del pelo (los huevos nuevos se encuentran cerca de las raíces del pelo por lo que es importante colocar los dientes muy cerca del cuero cabelludo). Asegúrese de que los dientes estén bien incrustados en el pelo mientras peina.

• Siempre peine hacia afuera de la cabeza.

• Retire las liendres de los dientes del peine frecuentemente con un pañuelo o toalla de papel.

• Quite las liendres restantes con la mano (usando un guante descartable).

• Tire todos los pañuelos o toallas en una bolsa de plástico sellada y deséchela de inmediato para evitar que los piojos regresen.

• Sujete nuevamente el mechón con una horquilla o hebilla.

• Levante otro mechón de 1-2" con gel y repita el proceso.

• Cuando haya peinado y sujetado una sección con gel, aplique el Gel Removedor de Huevos y Liendres a otra sección de pelo. Continúe peinando mechones de 1-2” por vez hasta que toda la cabeza haya sido peinada y el pelo esté sujetado.

• Mantenga el pelo húmedo mientras lo peina. Si el cabello se seca mientras lo peina, humedézcalo un poco con agua y vuelva a aplicar el Gel Removedor de Huevos y Liendres según sea necesario.

• Una vez que haya peinado y sujetado todo el cabello, quite todas las horquillas o hebillas y busque de nuevo minuciosamente las liendres. Vuelva a peinar si es necesario. Enjuague el pelo con abundante agua tibia. Si lo desea, también puede lavar el cabello con un champú común.

* Las liendres son cáscaras de huevos vacías que dejan los piojos cuando salen de los huevos.

Paso 3: Control

Aerosol para el Control de Piojos

• Use el Aerosol para el Control de Piojos para matar piojos y sus huevos en colchones, muebles, interiores de vehículos y otros artículos no lavables.

• Use el Aerosol para el Control de Piojos para matar piojos y sus huevos en colchones, muebles, interiores de vehículos y otros artículos no lavables. Un aerosol desinfectante común no mata los piojos y sus huevos.

• Luego de pulverizar el área infectada, pase la aspiradora en alfombras y tapetes. Arroje a la basura las bolsas de la aspiradora después de usarlas.

• Lave ropas, toallas, sombreros lavables, bufandas, abrigos y sábanas con agua caliente. Séquelos a temperatura alta durante al menos 20 minutos.

• Limpie en seco los artículos no lavables.

• Los peines y cepillos personales deben ser desinfectados sumergiéndolos en agua caliente (más de 130º F) (54º C) durante al menos 10 minutos.

• Coloque los juguetes rellenos en bolsas de plástico y séllelas por 4 semanas.

• Lista de verificación de desinfección

- Tapizados de vehículos y del hogar

- Colchones, almohadas, fundas

- Sábanas

- Toallas

- Animales rellenos, juguetes

- Auriculares

- Sombreros

- Vinchas

- Cascos de ciclista/cascos deportivos

- Abrigos, bufandas, orejeras, guantes

- Alfombras para juegos

- Ropa

- Broches/accesorios para el pelo

- Ruleros

- Peines y cepillos

- Gorras de béisbol.

Verificación Diaria

PARA PREVENIR LA REINFECCIÓN:

• Inspeccione cuidadosamente al miembro de la familia infectado a diario durante 2 semanas al menos. Si ve huevos o liendres, repita el Paso 2.

• Revise a otros miembros de la familia y busque piojos de la cabeza. Si alguien de la familia está infectado, siga el Paso 1 y el Paso 2. Repita el Paso 3 con todos los artículos u objetos con los que haya estado en contacto.

Segunda Aplicación

Repita los mismos procedimientos dentro de los 7-10 días del

Paso 1: Tratar y del Paso 2: Remover

Puede haber algunos huevos que no hayan sido removidos durante el primer tratamiento.

Estos huevos eclosionarán y deben ser eliminados con el segundo tratamiento.

Si la infestación continúa, consulte al médico por otros tratamientos.

¿Lo sabía?

Piojos de la cabeza

• ponen pequeños huevos blancos (liendres) en los cabellos cerca del cuero cabelludo.

• las liendres son más fáciles de encontrar en la nuca y detrás de las orejas.

• desinfecte sombreros, vinchas, bufandas, abrigos, toallas y sábanas lavándolos en el lavarropas con agua caliente (más de 54° C (130° F)), luego usando el ciclo de secado más caliente durante al menos 20 minutos.

• los artículos que no se pueden lavar (cubrecamas, mantas, almohadas, juguetes rellenos, etc.) deben ser lavados en seco o sellados en una bolsa plástica durante 4 semanas, luego hay que sacarlos fuera de la casa y sacudirlos con fuerza antes de volver a usarlos.

• los artículos que no se pueden lavar, limpiar en seco o guardar se puedenlos puede pulverizar con un producto diseñado para este fin.

• sumerja todos los peines y cepillos en agua caliente (más de 54° C (130° F)) durante 10 minutos por los menos.

• pase la aspiradora en alfombras, colchones, muebles con tapizados y asientos de vehículos que hayan sido usados por las personas afectadas.

Piojos del pubis (ladillas)

• pueden transmitirse por contacto sexual. Los compañeros sexuales deben ser tratados simultáneamente para evitar la reinfección.

• los piojos son muy pequeños y parecen puntos marrones o grises sobre la piel.

• usualmente causan picazón intensa y ponen pequeños huevos blancos (liendres) en el vello por lo general cerca de la superficie de la piel.

• pueden encontrarse en los vellos de la ingle, los muslos, el torso y las axilas y en ocasiones en la barba y el bigote.

• desinfecte la ropa interior lavándola en el lavarropas con agua caliente (más de 54° C (130° F)), luego use el ciclo de secado de temperatura más alta durante al menos 20 minutos.

Piojos del cuerpo

• los piojos del cuerpo y sus huevos (liendres) se encuentran por lo general en las costuras de la ropa particularmente en el área de la cintura y las axilas.

• los piojos del cuerpo se alimentan en la piel y luego regresan a la ropa a depositar sus huevos

• desinfecte la ropa lavándola en el lavarropas con agua caliente (más de 54° C (130° F)), luego use el ciclo de secado de temperatura más alta durante al menos 20 minutos.

• no selle la ropa en bolsas plásticas ya que las liendres pueden permanecer latentes hasta por 30 días.

Guarde este prospecto para futuras consultas.

Guarde el envase de cartón para contar con información importante acerca del producto.

Champú para la pediculosis

Componentes

Ingredientes activos Uso

Butóxido de piperonilo 4%.................................................................Tratamiento para la pediculosis

Extracto de piretro

(equivalente a 0,33% piretrinas)........................................................Tratamiento para la pediculosis

Usos tratamiento para piojos de la cabeza, púbicos (ladillas) y del cuerpo.

Precauciones

Sólo para uso externo.

No usar

- cerca de los ojos. • dentro de la nariz, la boca o la vagina.
- en piojos en las cejas o pestañas. Consulte a un médico si tiene piojos en estas zonas.

Consulte al médico antes de usar el producto si es •alérgico a la ambrosía. Puede causar dificultad para respirar o un ataque de asma.

Cuando use esteproducto

- mantenga los ojos bien cerrados y protéjalos con un paño o toalla,
- si le entra producto en los ojos, enjuáguelos con agua de inmediato,
- puede causar picazón o enrojecimiento del cuero cabelludo.

Deje de usar el producto y consulte al médico en caso de

- presentar dificultades para respirar,
- tener los ojos irritados,
- continuar la irritación de la piel o del cuero cabelludo o en caso de infección.

Mantener fuera del alcance de los niños. En caso de ingerir el producto, consiga ayuda médica o contacte al Centro de Toxicología de inmediato. (1-800-222-1222)

Instrucciones

Agitar bien antes de usar.

- Importante: Lea las precauciones antes de usar el producto.

Otrainformación

- almacenar a 20°-25° C (68°-77° F).
- Ingredientes inactivos alcohol bencílico, isoparafina C13-C14, fragancia, polioxietileno 1,1,3,3-tetrametil butil) fenil éter, agua purificada, goma xantano.

¿Quiere hacernos alguna pregunta o comentario? 1-800-719-9260

Gel Removedor de Huevos y Liendres

Componentes del producto

Uso para remover más rápido y fácil los huevos y las liendres.

Precauciones

Sólo para uso externo. Mantener fuera del alcance de los niños.

Ingredientes: agua purificada, glicerina, hidroxietilcelulosa, cloruro de PG-hidroxietilcelulosa cocodimonio, polisorbato 20, DMDM hidantoína, fragancia, butilcarbamato de yodopropinilo.

Almacenar a 20°-25° C (68°-77° F).

Aerosol para el Control de Piojos

Componentes del producto

INGREDIENTE ACTIVO:

*Permetrina…………………………………………………………………………………………………………………….0.50%

**OTROS INGREDIENTES:...................................................................................99.50%

100.00%

*Proporción cis/trans: Mínimo 35% (+/-) cis y Máximo 65% (+/-) trans.

**Contiene petróleo destilado.

AVISOS DE PRECAUCIÓN

PELIGROS PARA LOS HUMANOS

PRECAUCIÓN: Es peligroso si se traga el producto o si es absorbido por la piel. Evite la inhalación del rocío del aerosol. Puede causar irritación a los ojos. Evite el contacto con la piel, los ojos o la ropa. Lavarse con abundante agua y jabón luego de manipular el producto. Evitar la contaminación de alimentos para animalesganado y productos alimenticios.

RIESGOS FÍSICOS O QUÍMICOS

Contenido bajo presión. No usar ni almacenar cerca de fuentes de calor o de la llama expuesta. No perforar ni incinerar el envase. La exposición a temperaturas mayores a 130° F (54° C) puede causar que el envase explote.

PRIMEROS AUXILIOS

Llamar al Centro de Toxicología o a un médico de inmediato para recibir asesoramiento sobre el tratamiento a seguir. Tenga el envase o la etiqueta del producto a mano cuando llame al Centro de Toxicología, al médico o al solicitar tratamiento médico.

En caso de ingesta:

- Llame inmediatamente al Centro de Toxicología o a un médico.
- No provoque el vómito a menos que el Centro de Toxicología o un médico se lo indiquen.
- No le dée ningún líquido a la persona.
- No le dée nada por vía oral a una persona inconsciente.

Si el producto toma contacto con los ojos:

- Deje abiertos los ojos y enjuáguelos con agua de forma suave y despacio entre 15 y 20 minutos.
- Quítese los lentes de contacto, si tiene, después de los primeros 5 minutos, luego continúe enjuagándose los ojos.

En caso de inhalación:

- Lleve a la persona a un lugar con aire fresco.
- Si la persona no respira, llame al 911 o a una ambulancia, luego hágale respiración artificial, preferiblemente boca a boca, de ser posible.

Si el producto toma contacto con la piel o la ropa:

- Quítese la ropa contaminada.
- Enjuague la piel de inmediato con abundante agua durante 15 a 20 minutos.

AVISO PARA EL MÉDICO

Contiene petróleo destilado – el vómito puede causar neumonía por aspiración.

INSTRUCCIONES DE USO

Constituye una violación a las leyes federales el usar este producto en una manera que sea inconsistente con lo que se indica en la etiqueta. Cambie de lugar mascotas y aves y cubra peceras antes de usar el aerosol o de aplicarlo sobre superficies.

Este producto no es apto para ser usado en humanos. En caso de infestación de piojos en humanos, utilice un producto apto para ser usado en humanos. Salga de la habitación después del tratamiento y ventílela antes de volver a ingresar.

No permita que niños o mascotas tomen contacto con áreas tratadas hasta que las superficies estén secas.

AGITAR BIEN ANTES DE USAR.

Quite la tapa protectora. Mantenga el envase en posición vertical y rocíe desde una distancia de 8-10 pulgadas (20-25 centímetros). Las personas que padecen asma o alergias graves deben consultar a su médico antes de usar este producto y otra persona debe aplicárselo.

Para matar piojos y larvas: Rocíe en un lugar poco notorio para probar si el producto no destiñe o decolora. Inspeccione nuevamente después de que se seque, luego proceda a rociar toda la zona que deba ser tratada. Mantenga el envase en posición vertical con la boquilla lejos de usted. Presione la válvula y rocíe a una distancia entre 8 y 10 pulgadas (20 a 25 centímetros). Rocíe cada pie cuadrado (0,09 metro cuadrado) durante tres segundos. Aplique hasta que la superficie quede húmeda pero no empapada. Aplique solo en aquellos artículos o ropa de cama, incluidos colchones y muebles, que no puedan ser lavados ni limpiados en seco. No lo use en fundas de almohadas, sábanas o ropa. Deje que todos los artículos pulverizados se sequen bien antes de usarlos.

ALMACENAMIENTO Y ELIMINACIÓN

Almacenamiento: Guardar en un lugar fresco y seco, lejos del alcance de niños o mascotas y apartado de fuentes de calor, chispas o llamas expuestas. No transportar ni almacenar a temperaturas menores a 32° F (0° C).

Eliminación del envase: No perforar ni incinerar.

Si está vacío: Colóquelo en la basura u ofrézcalo para ser reciclado si es posible.

Si está parcialmente lleno: Llame a su servicio de desechos sólidos o al 1-800-CLEANUP para recibir instrucciones sobre cómo eliminar el producto. Nunca arroje el producto sin usar en ningún desagüe interior o exterior.

AVISO: El comprador asume toda la responsabilidad por la seguridad y el uso del producto que no sea conforme a las instrucciones.

Véase el envase de cartón para obtener los números de la Agencia de Control Ambiental.